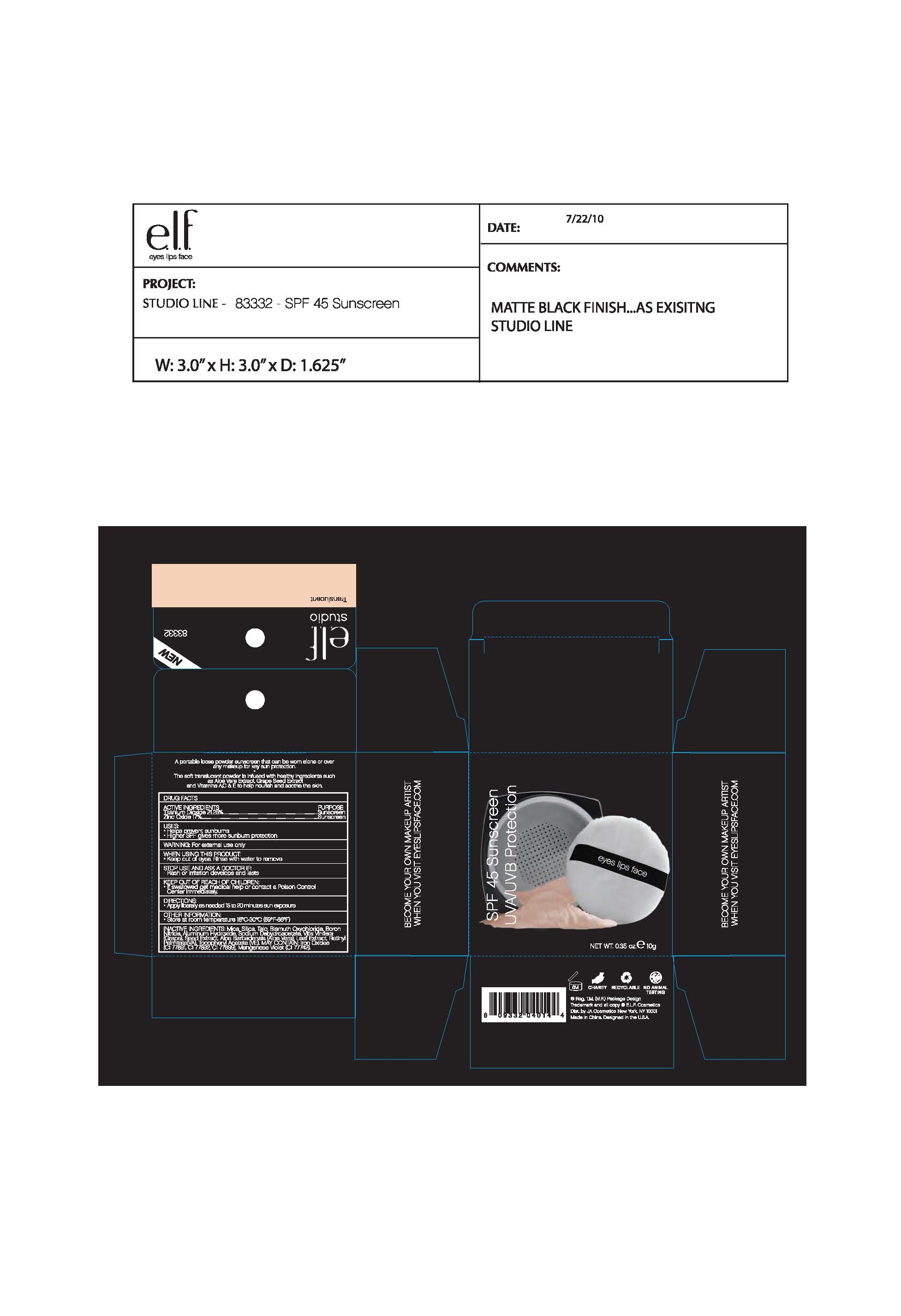 DRUG LABEL: ELF SPF 45 Sunscreen UVA/UVB Protection
NDC: 52664-010 | Form: POWDER
Manufacturer: Hangzhou Facecare Cosmetics Co., Ltd.
Category: otc | Type: HUMAN OTC DRUG LABEL
Date: 20101117

ACTIVE INGREDIENTS: TITANIUM DIOXIDE 21.25 g/100 g; ZINC OXIDE 17 g/100 g
INACTIVE INGREDIENTS: BISMUTH OXYCHLORIDE; .ALPHA.-TOCOPHEROL ACETATE, DL-; MICA; FERRIC OXIDE RED; FERRIC OXIDE YELLOW; FERROSOFERRIC OXIDE; SILICON DIOXIDE; TALC; ALUMINUM HYDROXIDE; SODIUM DEHYDROACETATE; ALOE VERA LEAF; GRAPE SEED OIL; VITAMIN A PALMITATE

Drug Fact

Active Ingredient:

Titanium Dioxide: 21.25%

Zinc Oxide: 17%

Purpose:

Sunscreen

Uses:

Help prevent sunburns

Higher SPF gives more sunburn protection

Warning:

For external use only

When Using This Product:

Keep out of eyes. Rinse with water to remove.

Stop Use and Ask a Doctor if:

Rash or irritation develops and lasts

Keep Out of Reach of Children:

If swallowed get medical help or contact a Poison Control Center immediately

Directions:

Apply as needed for 15-20 minutes of sun exposure

STORAGE AND HANDLING

Other Imformation:

Store at room temperature 15-30C (59-86F)

Inactive Ingredient:

Mica, Silica, Talc, Bismuth Oxychloride, Boron Nitride, Aluminum Hydroxide, Sodium Dehydroacetate, Vitis Vinifera (Grape) Seed Extract, Aloe Barbadensis Leaf Extract, Retinyl Palmitate (VA), Tocopheryl Acetate (VE)

May contain:

Iron Oxides (CI 77491, CI 77492, CI 77499), Manganese Violet (CI 77742)

PACKAGE LABEL

labe